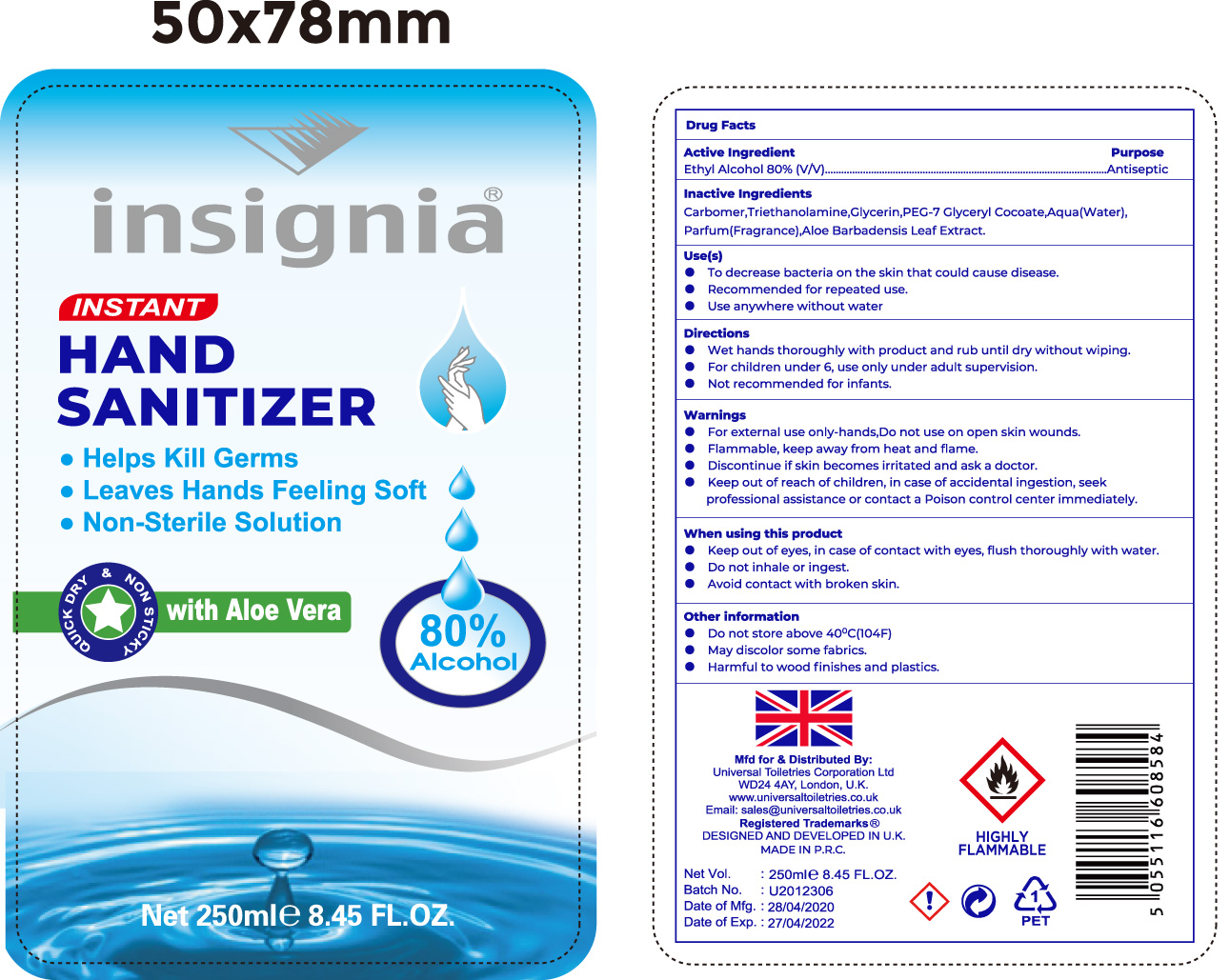 DRUG LABEL: Insignia Instant Hand Sanitizer
NDC: 75410-003 | Form: SOLUTION
Manufacturer: Yiwu Story of Love Cosmetic Co., Ltd
Category: otc | Type: HUMAN OTC DRUG LABEL
Date: 20200608

ACTIVE INGREDIENTS: ALCOHOL 80 mL/100 mL
INACTIVE INGREDIENTS: GLYCERIN; CARBOMER 934; TRIETHANOLAMINE SULFATE; PEG-7 GLYCERYL COCOATE; ALOE VERA LEAF

Active Ingredient(s)

Ethyl Alcohol 80% v/v

Purpose

Antiseptic

Use

To decrease bacteria on the skin that could cause disease

Recommended for repeated use

To use anywhere without water

Warnings

For external use only. Flammable. Keep away from heat and flame

Discontinue if skin becomes irritated and ask a doctor

When using this product keep out of eyes. In case of contact with eyes, flush thoroughly with water.

Do not inhale or ingest

Avoid contact with broken skin

Keep out of reach of children. In case of accidental ingest, seek professional assist or contact a Poison Control Center immediately.

Directions

- Wet hands thoroughly with product and rub until dry without wiping
- For children under 6, use only under adult supervision
- Not recommended for infants

Other information

- Do not store above 40C (104F)
- May discolor wood or fabrics
- Harmful to wood finishes or plastics

Inactive ingredients

Carbomer, Triethanolamine, Glycerin, PEG-7 glyceryl CoCoate, Water, Parfum (Fragrance), Aloe barbadensis leaf extract